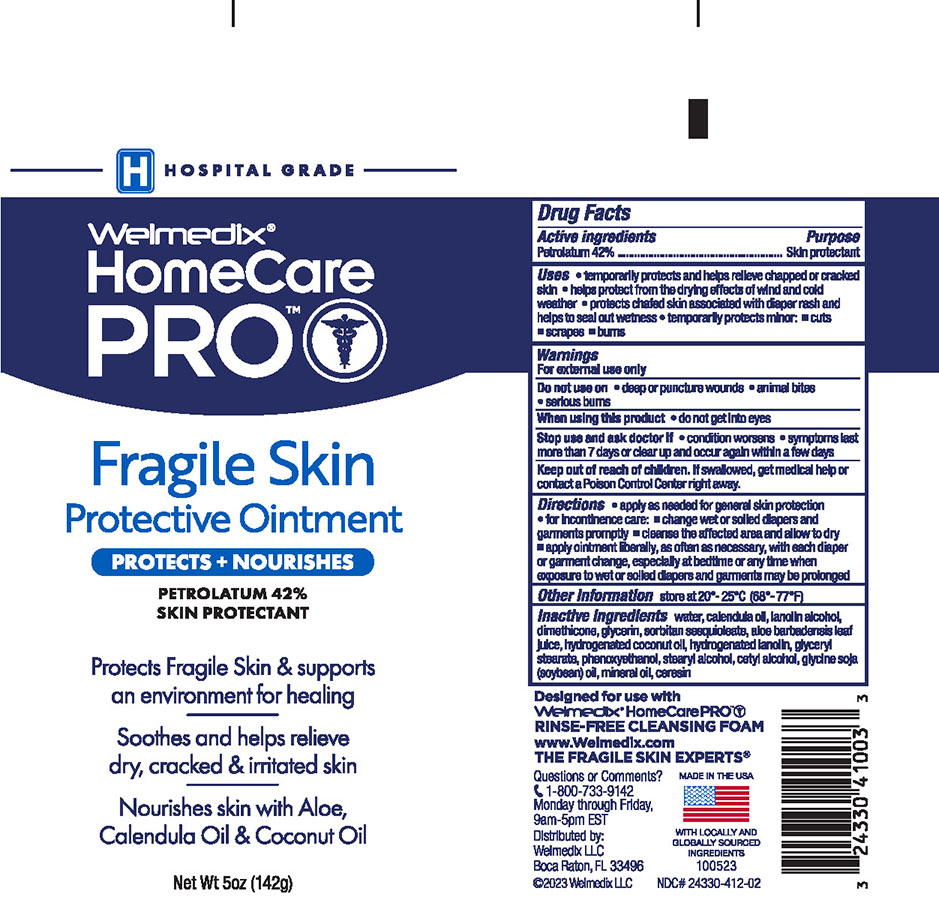 DRUG LABEL: Welmedix HomeCare PRO Fragile Skin Protectant
NDC: 24330-412 | Form: OINTMENT
Manufacturer: Welmedix LLC
Category: otc | Type: HUMAN OTC DRUG LABEL
Date: 20231205

ACTIVE INGREDIENTS: PETROLATUM 42 g/100 g
INACTIVE INGREDIENTS: ALOE VERA LEAF; CALENDULA OFFICINALIS FLOWER; CERESIN; CETYL ALCOHOL; DIMETHICONE; WATER; GLYCERIN; GLYCERYL MONOSTEARATE; SOY STEROL; HYDROGENATED COCONUT OIL; LANOLIN; LANOLIN ALCOHOLS; MINERAL OIL; PHENOXYETHANOL; SORBITAN SESQUIOLEATE; STEARYL ALCOHOL

Welmedix® HomeCare PRO Fragile Skin Protective Ointment

Active ingredients

Petrolatum 42%

Purpose

Skin Protectant

Uses

- temporarily protects and helps relieve chapped or cracked skin
- helps protect from the drying effects of wind and cold weather
- helps treat and prevent diaper rash
- protects chafed skin associated with diaper rash and helps protect from wetness
- temporarily protects: • minor cuts • scrapes • burns

Warnings

For external use only

Do not use on

- deep or puncture wounds
- animal bites
- serious burns

Stop use and ask a doctor if

- condition worsens
- symptoms last more than 7 days or clear up and occur again within a few days.

Keep out of reach of children

If swallowed, get medical help or consult a Poison Control Center right away.

Directions:

For general skin protection: apply as needed.

For incontinence care: change wet and soiled diapers and garments promptly. • Cleanse the affected area and allow to dry. • Apply ointment liberally, as often as necessary, especially at bedtime or any time when exposure to wet, moist or soiled garments may be prolonged.

Other Information:

Store at 20-25° C (68-77° F)

Inactive ingredients

water, calendula oil, lanolin alcohol, dimethicone, glycerin, sorbitan sesquioleatem, aloe barbadensis leaf juice, hydrogenated coconut oil, hydrogenated lanolin, glyceryl stearate, phenoxyethanol, stearyl alcohol, cetyl alcohol, glycine soja (soybean) oil, mineral oil, ceresin

Principal Display Panel

PROTECTS +
NOURISHES

Hospital
Grade

Welmedix®
HomeCare
PRO

FRAGILE SKIN
PROTECTIVE OINTMENT

PETROLATUM 42%

Protects fragile skin &
creates an environment
for healing

Soothes and helps
relieve dry, cracked
and irritated skin

Nourishes skin with
Aloe, Calendula Oil
and Coconut Oil

Net Wt 5 oz (142g)